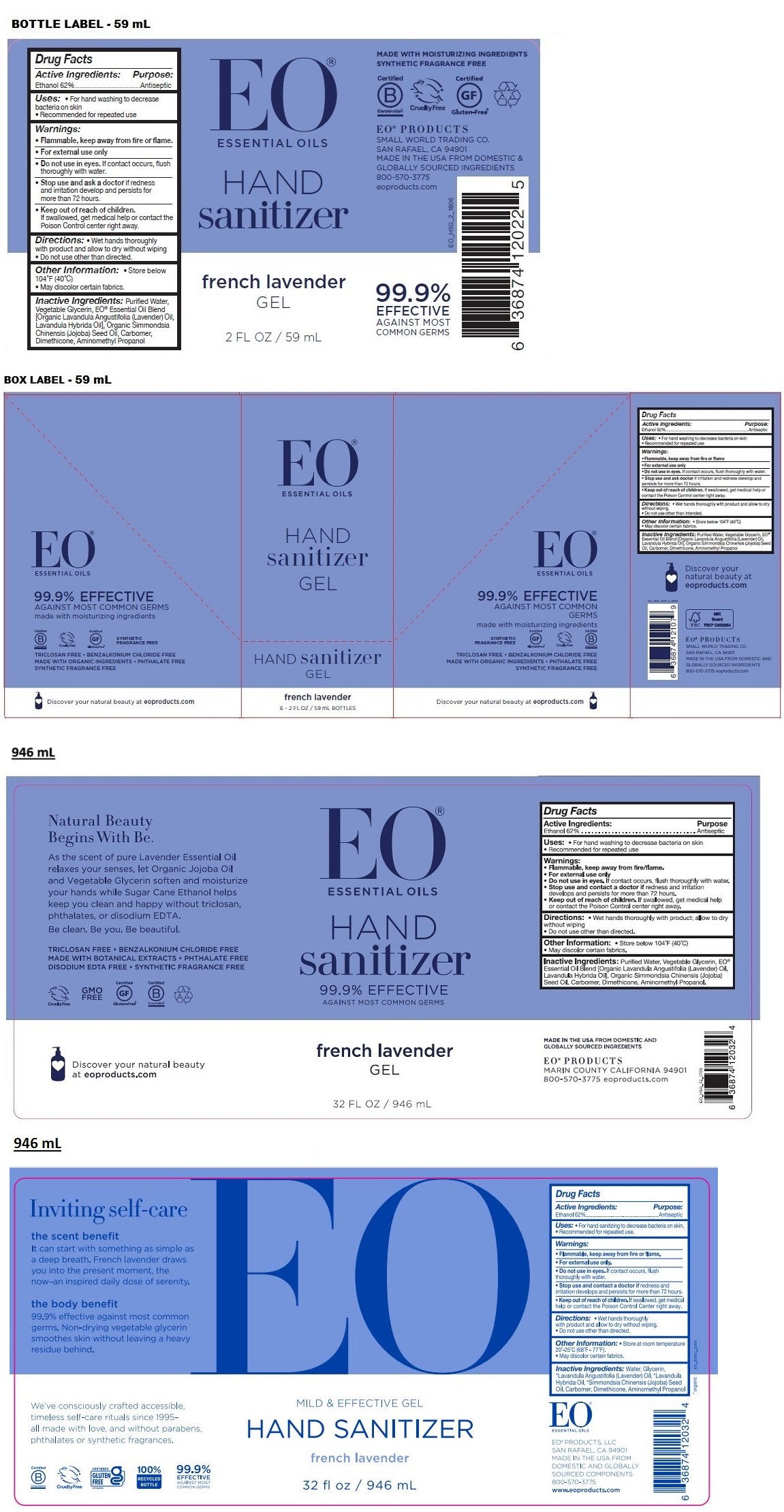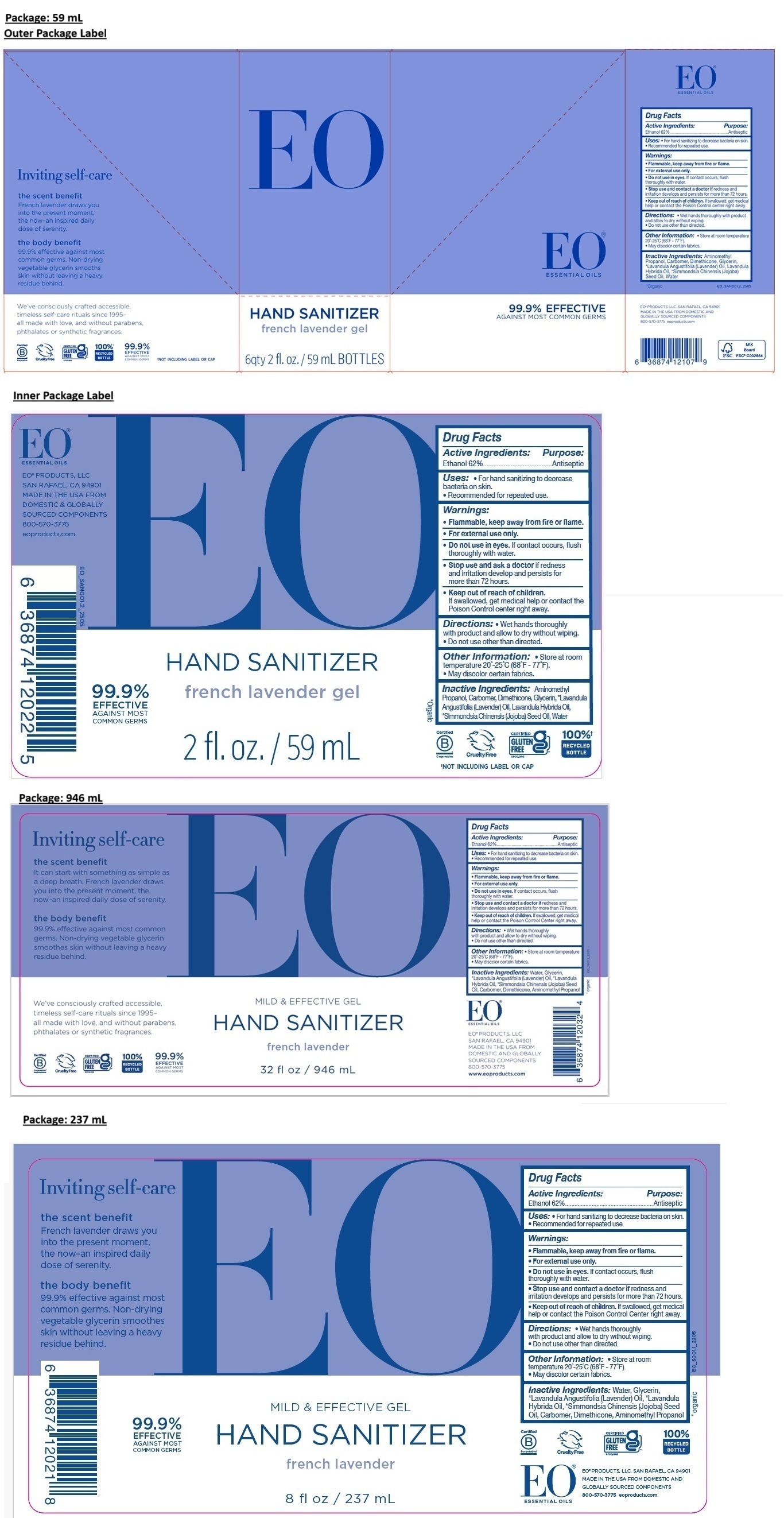 DRUG LABEL: EO HAND SANITIZER
NDC: 54748-201 | Form: GEL
Manufacturer: EO Products, LLC
Category: otc | Type: HUMAN OTC DRUG LABEL
Date: 20251121

ACTIVE INGREDIENTS: ALCOHOL 62 mL/100 mL
INACTIVE INGREDIENTS: AMINOMETHYLPROPANOL; CARBOMER HOMOPOLYMER, UNSPECIFIED TYPE; DIMETHICONE, UNSPECIFIED; GLYCERIN; LAVENDER OIL; LAVANDIN OIL; JOJOBA OIL; WATER

EO HAND SANITIZER french lavender gel

Active Ingredients:

Ethanol 62%

Purpose:

Antiseptic

Uses:

• For hand sanitizing to decrease bacteria on skin.
• Recommended for repeated use.

Warnings:

• Flammable, keep away from fire or flame.
• For external use only.
• Do not use in eyes. If contact occurs, flush thoroughly with water.
• Stop use and contact a doctor if redness and irritation develops and persists for more than 72 hours.

• Keep out of reach of children. If swallowed, get medical help or contact the Poison Control center right away.

Directions:

• Wet hands thoroughly with product and allow to dry without wiping.
• Do not use other than directed.

Other Information:

• Store at room temperature 20°-25°C (68°F - 77°F).
• May discolor certain fabrics.

Inactive Ingredients:

Aminomethyl Propanol, Carbomer, Dimethicone, Glycerin, *Lavandula Angustifolia (Lavender) Oil, Lavandula Hybrida Oil, *Simmondsia Chinensis (Jojoba) Seed Oil, Water

*Organic

EO® ESSENTIAL OILS

99.9% EFFECTIVE AGAINST MOST COMMON GERMS

EO® PRODUCTS, LLC. SAN RAFAEL, CA 94901
MADE IN THE USA FROM DOMESTIC AND GLOBALLY SOURCED COMPONENTS
800-570-3775 eoproducts.com

Inviting self-care

the scent benefit
French lavender draws you into the present moment, the now–an inspired daily dose of serenity.

the body benefit
99.9% effective against most common germs. Non-drying vegetable glycerin smooths skin without leaving a heavy residue behind.

We’ve consciously crafted accessible, timeless self-care rituals since 1995– all made with love, and without parabens, phthalates or synthetic fragrances.

Cruelty Free

CERTIFIED GLUTEN FREE

MILD & EFFECTIVE GEL